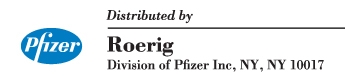 DRUG LABEL: Unknown
Manufacturer: Roerig
Category: prescription | Type: HUMAN PRESCRIPTION DRUG LABELING
Date: 20060407

TERRA-CORTRIL®
Terramycin® (oxytetracycline HCl)
—Cortril® (hydrocortisone acetate)
OPHTHALMIC SUSPENSION

DESCRIPTION

Terra-Cortril suspension combines the antibiotic, oxytetracycline HCl (C22H24N2O9•HCl) and the adrenocorticoid, hydrocortisone acetate (C23H32O6). Each ml of Terra-Cortril contains Terramycin (oxytetracycline HCl) equivalent to 5 mg of oxytetracycline, and 15 mg of Cortril (hydrocortisone acetate) incorporated in mineral oil with aluminum tristearate.

For Ophthalmic Use Only.

CLINICAL PHARMACOLOGY

Corticosteroids suppress the inflammatory response to a variety of agents and they probably delay or slow healing. Since corticoids may inhibit the body's defense mechanism against infection, a concomitant antimicrobial drug may be used when this inhibition is considered to be clinically significant in a particular case.

The anti-infective component in the combination is included to provide action against specific organisms susceptible to it.

Terramycin is considered active against the following microorganisms:

- Rickettsiae (Rocky Mountain spotted fever, typhus fever and the typhus group, Q fever, rickettsialpox and tick fevers),
- Mycoplasma pneumoniae (PPLO, Eaton Agent),
- Agents of psittacosis and ornithosis,
- Agents of lymphogranuloma venereum and granuloma inguinale,
- The spirochetal agent of relapsing fever (Borrelia recurrentis).

The following gram-negative microorganisms:

- Haemophilus ducreyi (chancroid),
- Pasteurella pestis and Pasteurella tularensis,
- Bartonella bacilliformis,
- Bacteroides species,
- Vibrio comma and Vibrio fetus,
- Brucella species (in conjunction with streptomycin).

Because many strains of the following groups of microorganisms have been shown to be resistant to tetracyclines, culture and susceptibility testing are recommended.

Oxytetracycline is indicated for treatment of infections caused by the following gram-negative microorganisms, when bacteriologic testing indicates appropriate susceptibility to the drug:

- Escherichia coli,
- Enterobacter aerogenes (formerly Aerobacter aerogenes),
- Shigella species,
- Mima species and Herellea species,
- Haemophilus influenzae (respiratory infections),
- Klebsiella species (respiratory and urinary infections).

Oxytetracycline is indicated for treatment of infections caused by the following gram-positive microorganisms when bacteriologic testing indicates appropriate susceptibility to the drug:

Streptococcus species:

Up to 44 percent of strains of Streptococcus pyogenes and 74 percent of Streptococcus faecalis have been found to be resistant to tetracycline drugs. Therefore, tetracyclines should not be used for streptococcal disease unless the organism has been demonstrated to be sensitive.

For upper respiratory infections due to Group A beta-hemolytic streptococci, pencillin is the usual drug of choice, including prophylaxis of rheumatic fever.

Diplococcus pneumoniae,

Staphylococcus aureus, skin and soft tissue infections. Oxytetracycline is not the drug of choice in the treatment of any type of staphylococcal infections.

When penicillin is contraindicated, tetracyclines are alternative drugs in the treatment of infections due to:

- Neisseria gonorrhoeae,
- Treponema pallidum and Treponema pertenue (syphilis and yaws),
- Listeria monocytogenes,
- Clostridium species,
- Bacillus anthracis,
- Fusobacterium fusiforme (Vincent's infection),
- Actinomyces species.

Tetracyclines are indicated in the treatment of trachoma, although the infectious agent is not always eliminated, as judged by immunofluorescence.

Inclusion conjunctivitis may be treated with oral tetracyclines or with a combination of oral and topical agents.

When a decision to administer both a corticoid and an antimicrobial is made, the administration of such drugs in combination has the advantage of greater patient compliance and convenience, with the added assurance that the appropriate dosage of both drugs is administered, plus assured compatibility of ingredients when both types of drug are in the same formulation and, particularly, that the correct volume of drug is delivered and retained.

The relative potency of corticosteroids depends on the molecular structure, concentration, and release from the vehicle.

INDICATIONS AND USAGE

For steroid-responsive inflammatory ocular conditions for which a corticosteroid is indicated and where bacterial infection or a risk of bacterial ocular infection exists.

Ocular steroids are indicated in inflammatory conditions of the palpebral and bulbar conjunctiva, cornea, and anterior segment of the globe where the inherent risk of steroid use in certain infective conjunctivitides is accepted to obtain a diminution in edema and inflammation. They are also indicated in chronic anterior uveitis and corneal injury from chemical radiation, thermal burns, or penetration of foreign bodies.

The use of a combination drug with an anti-infective component is indicated where the risk of infection is high or where there is an expectation that potentially dangerous numbers of bacteria will be present in the eye.

The particular anti-infective drug in this product is active against the following common bacterial eye pathogens:

- Staphylococcus aureus
- Streptococci, including Streptococcus pneumoniae
- Escherichia coli
- Neisseria species

The product does not provide adequate coverage against:

- Haemophilus influenzae
- Klebsiella/Enterobacter species
- Pseudomonas aeruginosa
- Serratia marcescens

CONTRAINDICATIONS

Epithelial herpes simplex keratitis (dendritic keratitis), vaccinia, varicella, and many other viral diseases of the cornea and conjunctiva. Mycobacterial infection of the eye. Fungal diseases of ocular structures. Hypersensitivity to a component of the medication. (Hypersensitivity to the antibiotic component occurs at a higher rate than for other components.)

The use of these combinations is always contraindicated after uncomplicated removal of a corneal foreign body.

WARNINGS

Prolonged use may result in glaucoma, with damage to the optic nerve, defects in visual acuity and fields of vision, and posterior subcapsular cataract formation. Prolonged use may suppress the host response and thus increase the hazard of secondary ocular infections. In those diseases causing thinning of the cornea or sclera, perforations have been known to occur with the use of topical steroids. In acute purulent conditions of the eye, steroids may mask infection or enhance existing infection. If these products are used for 10 days or longer, intraocular pressure should be routinely monitored even though it may be difficult in children and uncooperative patients.

Employment of steroid medication in the treatment of herpes simplex requires great caution.

PRECAUTIONS

The initial prescription and renewal of the medication order beyond 20 milliliters should be made by a physician only after examination of the patient with the aid of magnification, such as slit lamp biomicroscopy and, where appropriate, fluorescein staining.

The possibility of persistent fungal infections of the cornea should be considered after prolonged steroid dosing.

ADVERSE REACTIONS

Adverse reactions have occurred with steroid/anti-infective combination drugs which can be attributed to the steroid component, the anti-infective component, or the combination. Exact incidence figures are not available since no denominator of treated patients is available.

Reactions occurring most often from the presence of the anti-infective ingredient are allergic sensitizations. The reactions due to the steroid component in decreasing order of frequency are: elevation of intraocular pressure (IOP) with possible development of glaucoma, and infrequent optic nerve damage; posterior subcapsular cataract formation; and delayed wound healing.

Secondary Infection

The development of secondary infection has occurred after use of combinations containing steroids and antimicrobials. Fungal infections of the cornea are particularly prone to develop coincidentally with long-term applications of steroid. The possibility of fungal invasion must be considered in any persistent corneal ulceration where steroid treatment has been used.

Secondary bacterial ocular infection following suppression of host responses also occurs.

DOSAGE AND ADMINISTRATION

Instill 1 or 2 drops of Terra-Cortril Ophthalmic Suspension into the affected eye three times daily.

Not more than 20 milliliters should be prescribed initially and the prescription should not be refilled without further evaluation as outlined in "Precautions" above.

HOW SUPPLIED

Terra-Cortril Ophthalmic Suspension (NDC 0049-0670-48) is supplied in 5 ml vials with separate sterile dropper.

LAB-0194-2.0